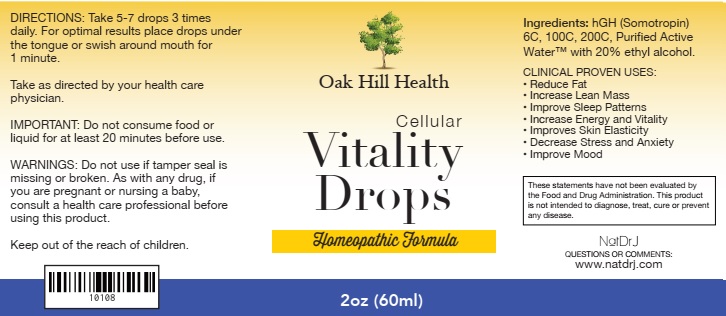 DRUG LABEL: Vitality Drops
NDC: 71559-305 | Form: LIQUID
Manufacturer: NaturoDRJ Enterprises
Category: homeopathic | Type: HUMAN PRESCRIPTION DRUG LABEL
Date: 20181226

ACTIVE INGREDIENTS: SOMATROPIN 6 [hp_C]/60 mL
INACTIVE INGREDIENTS: WATER; ALCOHOL

Vitality Drops

ACTIVE INGREDIENT

Ingredients: hGH (Somotropin) 6C, 100C, 200C

These statements have not been evaluated by the Food and Drug Administration. This product is not intended to diagnose, treat, cure or prevent any disease.

INDICATIONS AND USAGE

CLINICAL PROVEN USES:

• Reduce Fat

• Increase Lean Mass

• Improve Sleep Patterns

• Increase Energy and Vitality

• Improves Skin Elasticity

• Decrease Stress and Anxiety

• Improve Mood

WARNINGS

WARNINGS: Do not use if tamper seal is missing or broken. As with any drug, if you are pregnant or nursing a baby, consult a health care professional before using this product.

Keep out of reach of children.

DOSAGE AND ADMINISTRATION

DIRECTIONS: Take 5-7 drops 3 times daily. For optimal results place drops under the tongue or swish around mouth for 1 minute.

Take as directed by your health care physician.

OTHER SAFETY INFORMATION

IMPORTANT: Do not consume food or liquid for at least 20 minutes before use.

INACTIVE INGREDIENT

Purified Active Water™ with 20% ethyl alcohol.

QUESTIONS

NatDrJ

QUESTIONS OR COMMENTS:

www.natdrj.com

PACKAGE LABEL

Oak Hill Health

Cellular

Vitality

Drops

Homeopathic Formula

2oz (60ml)

PURPOSE

CLINICAL PROVEN USES:

• Reduce Fat

• Increase Lean Mass

• Improve Sleep Patterns

• Increase Energy and Vitality

• Improves Skin Elasticity

• Decrease Stress and Anxiety

• Improve Mood